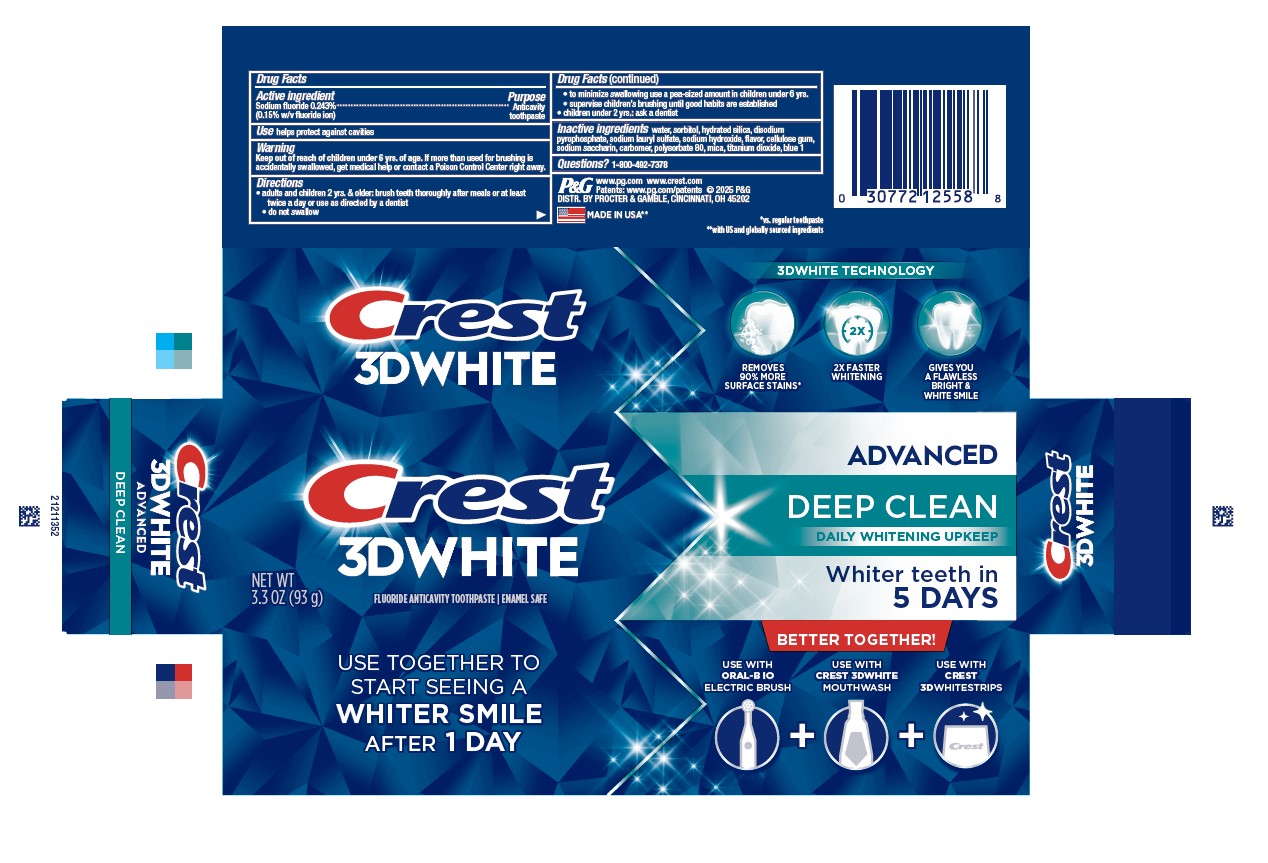 DRUG LABEL: Crest 3D White
NDC: 69423-836 | Form: PASTE, DENTIFRICE
Manufacturer: Procter & Gamble Manfuacturing Company
Category: otc | Type: HUMAN OTC DRUG LABEL
Date: 20250806

ACTIVE INGREDIENTS: SODIUM FLUORIDE 1.5 mg/1 g
INACTIVE INGREDIENTS: FD&C BLUE NO. 1; CARBOXYPOLYMETHYLENE; SODIUM ACID PYROPHOSPHATE; CARBOXYMETHYLCELLULOSE SODIUM; POLYSORBATE 80; WATER; SACCHARIN SODIUM; HYDRATED SILICA; SODIUM LAURYL SULFATE; TITANIUM DIOXIDE; SORBITOL; SODIUM HYDROXIDE; MICA

Crest®
3D White™
Advanced Deep Clean

Drug Facts

Active ingredient

Sodium fluoride 0.243% (0.15% w/v fluoride ion)

Purpose

Anticavity toothpaste

Use

helps protect against cavities

Warnings

Keep out of reach of children under 6 yrs. of age.If more than used for brushing is accidentally swallowed, get medical help or contact a Poison Control Center right away.

Directions

- adults and children 2 yrs. & older: brush teeth thoroughly after meals or at least twice a day or use as directed by a dentist
  - do not swallow
  - to minimize swallowing use a pea-sized amount in children under 6
  - supervise children's brushing until good habits are established
- children under 2 yrs.: ask a dentist

Inactive ingredients

water, sorbitol, hydrated silica, disodium pyrophosphate, sodium lauryl sulfate, sodium hydroxide, flavor, cellulose gum, sodium saccharin, carbomer, polysorbate 80, mica, titanium dioxide, blue 1

Questions?

1-800-492-7378

DISTR. BY PROCTER & GAMBLE,

CINCINNATI, OH 45202

PRINCIPAL DISPLAY PANEL - 93 g Carton

CREST

3D WHITE

ADVANCED

DEEP CLEAN

DAILY WHITENING UPKEEP

WHITER TEETH IN

5 DAYS

NET WT OZ (93 g)

fluoride anticavity toothpaste

enamel safe